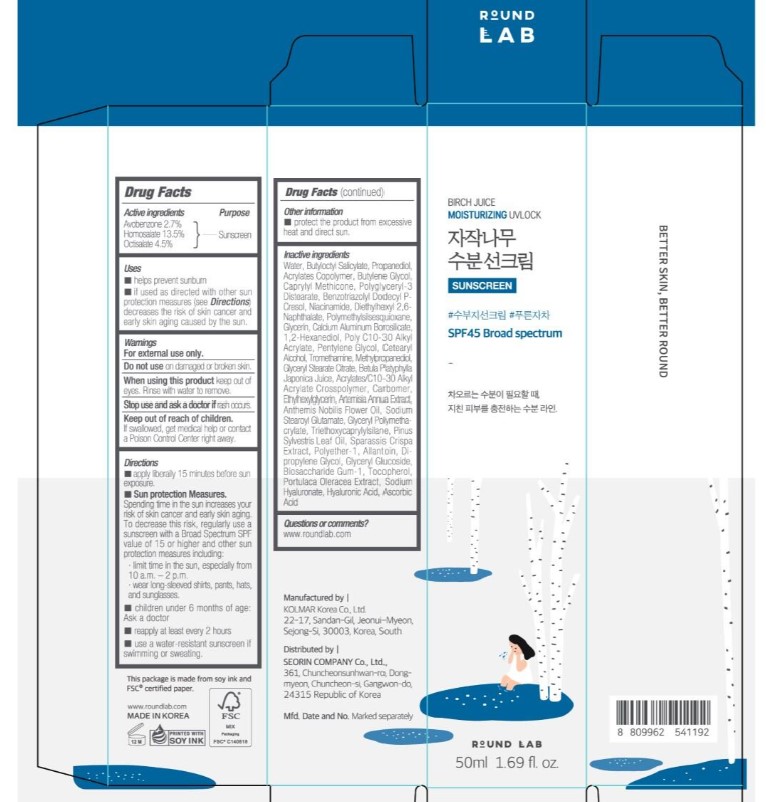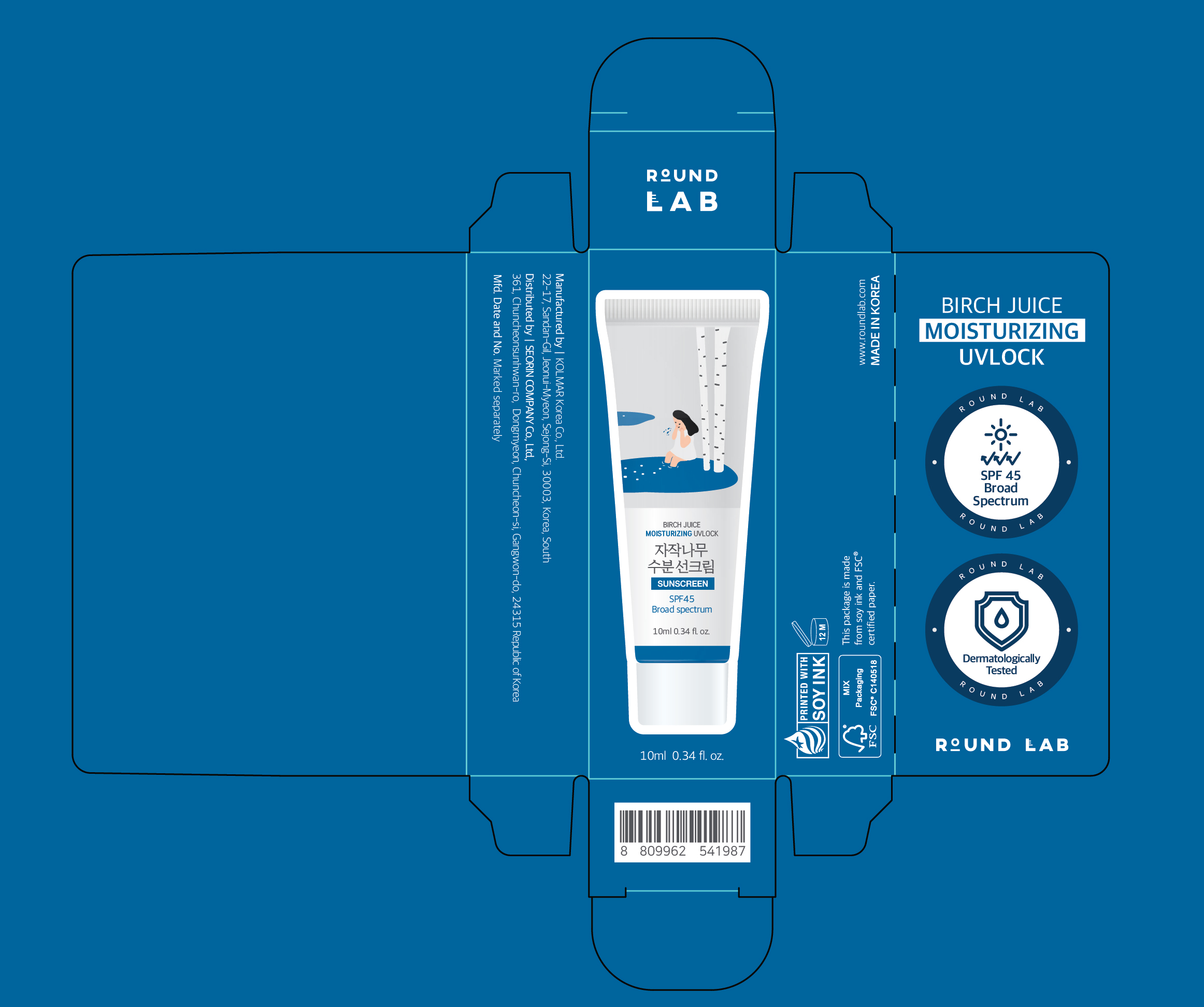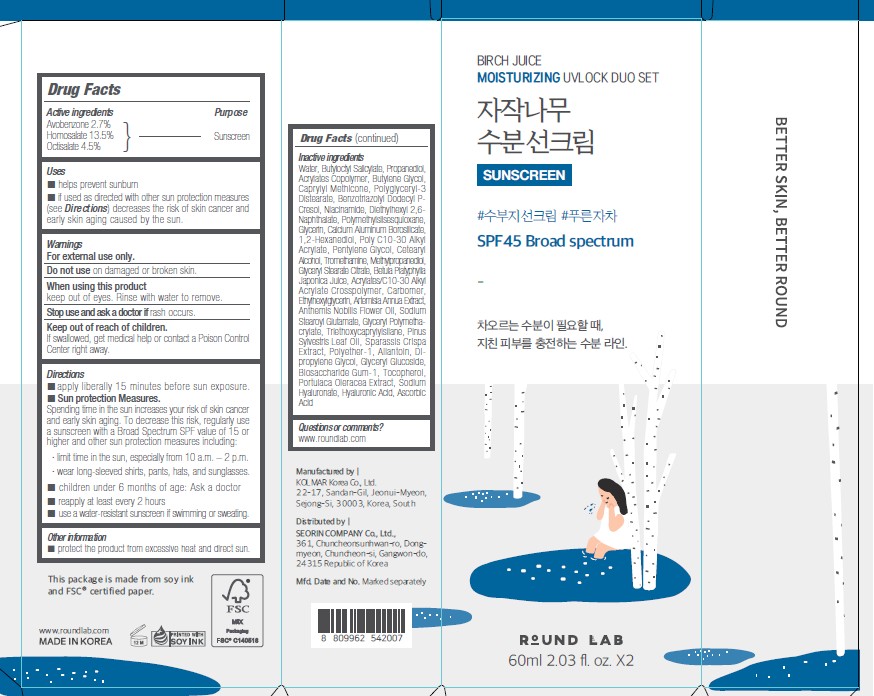 DRUG LABEL: ROUND LAB BIRCH JUICE MOISTURIZING UVLOCK SUNSCREEN SPF45 BROAD SPECTRUM
NDC: 84616-005 | Form: CREAM
Manufacturer: SEORIN COMPANY Co., Ltd.
Category: otc | Type: HUMAN OTC DRUG LABEL
Date: 20251030

ACTIVE INGREDIENTS: HOMOSALATE 13.5 g/100 mL; OCTISALATE 4.5 g/100 mL; AVOBENZONE 2.7 g/100 mL
INACTIVE INGREDIENTS: BENZOTRIAZOLYL DODECYL P-CRESOL; BIOSACCHARIDE GUM-1; TROMETHAMINE; HYALURONATE SODIUM; GLYCERYL STEARATE CITRATE; CHAMAEMELUM NOBILE FLOWER OIL; GLYCERYL POLYMETHACRYLATE (300000 MPA.S); TRIETHOXYCAPRYLYLSILANE; TOCOPHEROL; HYALURONIC ACID; SPARASSIS CRISPA FRUITING BODY; PURSLANE; WATER; BUTYLOCTYL SALICYLATE; PROPANEDIOL; BUTYL ACRYLATE/METHYL METHACRYLATE/METHACRYLIC ACID COPOLYMER (18000 MW); BUTYLENE GLYCOL; CAPRYLYL TRISILOXANE; POLYGLYCERYL-3 DISTEARATE; DIETHYLHEXYL 2,6-NAPHTHALATE; NIACINAMIDE; POLYMETHYLSILSESQUIOXANE (4.5 MICRONS); GLYCERIN; PINE NEEDLE OIL (PINUS SYLVESTRIS); CALCIUM ALUMINUM BOROSILICATE; 1,2-HEXANEDIOL; BEHENYL ACRYLATE POLYMER; PENTYLENE GLYCOL; CETOSTEARYL ALCOHOL; METHYLPROPANEDIOL; BETULA PLATYPHYLLA VAR. JAPONICA RESIN; ACRYLATES/C10-30 ALKYL ACRYLATE CROSSPOLYMER (60000 MPA.S); CARBOMER HOMOPOLYMER, UNSPECIFIED TYPE; ETHYLHEXYLGLYCERIN; ARTEMISIA ANNUA LEAF; SODIUM STEAROYL GLUTAMATE; DIPROPYLENE GLYCOL; ALLANTOIN; GLYCERYL GLUCOSIDE; ASCORBIC ACID; POLYETHER-1 (2800 MPA.S)

Round Lab
Birch Juice
Moisturizing UVLOCK
Sunscreen
SPF45 Broad Spectrum

Actives Ingredients

Avobenzone 2.7%

Homosalate 13.5%

Octisalate 4.5%

Purpose

Sunscreen

Uses

helps prevent sunburn
if used as directed with other sun protection measures (see Directions) decreases the risk of skin cancer and early skin aging caused by the sun.

Warnings

For external use only.

Do not use on damaged or broken skin.

When using this product keep out of eyes. Rinse with water to remove

Stop use and ask a doctor if rash occurs

Keep out of reach of children.

If swallowed, get medical help or contact a Poison Control Center right away.

Directions

- apply liberally and evenly 15 minutes before sun exposure.
- Sun protection measures.

Spending time in the sun increases your risk of skin cancer and early aging. To decrease this risk, regularly use a sunscreen with a Broad Spectrum SPF value of 15 or higher and other sun protection measures including: limit time in the sun, especially from 10 a.m. - 2 p.m., wear long-sleeved shirts, pants, hats, and sunglasses

- children under 6 months of age: Ask a doctor
- reapply at least every 2 hours.
- use a water-resistant sunscreen if swimming or sweating

Other Information

protect the product from excessive heat and direct sun

Inactive ingredients

Water, Butyloctyl Salicylate, Propanediol, Acrylates Copolymer, Butylene Glycol, Caprylyl Methicone, Polyglyceryl-3 Distearate, Benzotriazolyl Dodecyl P-Cresol, Niacinamide, Diethylhexyl 2,6-Naphthalate, Polymethylsisesquioxane, Glycerin, Calcium Aluminum Borosilicate, 1,2-Hexanediol, Poly C10-30 Alkyl Acrylate, Pentylene Glycol, Cetearyl Aloohol, Tromethamine, Methy propanediol, Glyceryl Stearate Citrate, Betula Platyphylla Japonica Juice, Acrylates/C10-30 Alkyl Acrylate Crosspolymer, Carbomer, Ethylhexylglycerin, Artemisia Annua Extract, Anthemis Nobilis Flower Oil, Sodium Stearoyl Glutamate, Glyceryl Polymethacrylate, Triethoxycaprylylsilane, Pinus Sylvestris Leaf Oil, Sparassis Crispa Extract, Polyether-1, Allantoin, Di-propylene Glycol, Glyceryl Glucoside, Biosaccharide Gum-1, Tocopherol, Portulaca Oleracea Extract, Sodium Hyaluronate, Hyaluronic Acid, Ascorbic Acid

Questions or comments?

www.roundlab.com

PACKAGE LABEL

Round Lab

Birch Juice

Moisturizing UVLOCK

Sunscreen

SPF45 Broad Spectrum

50 mL 1.69 fl. oz.

PACKAGE LABEL

BIRCH JUICE
MOISTURIZING UVLOCK

SUNSCREEN

SPF45

Broad Spectrum

10mL 0.34 fl.oz.

PACKAGE LABEL

BIRCH JUICE

MOISTURIZING UVLOCK DUO SET

SUNSCREEN

SPF45 Broad Spectrum

Round Lab

60ml 2.03fl. oz. X2